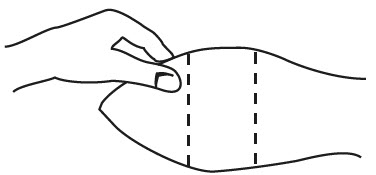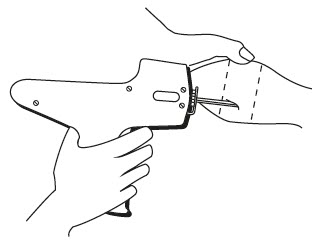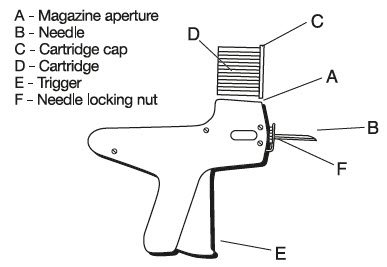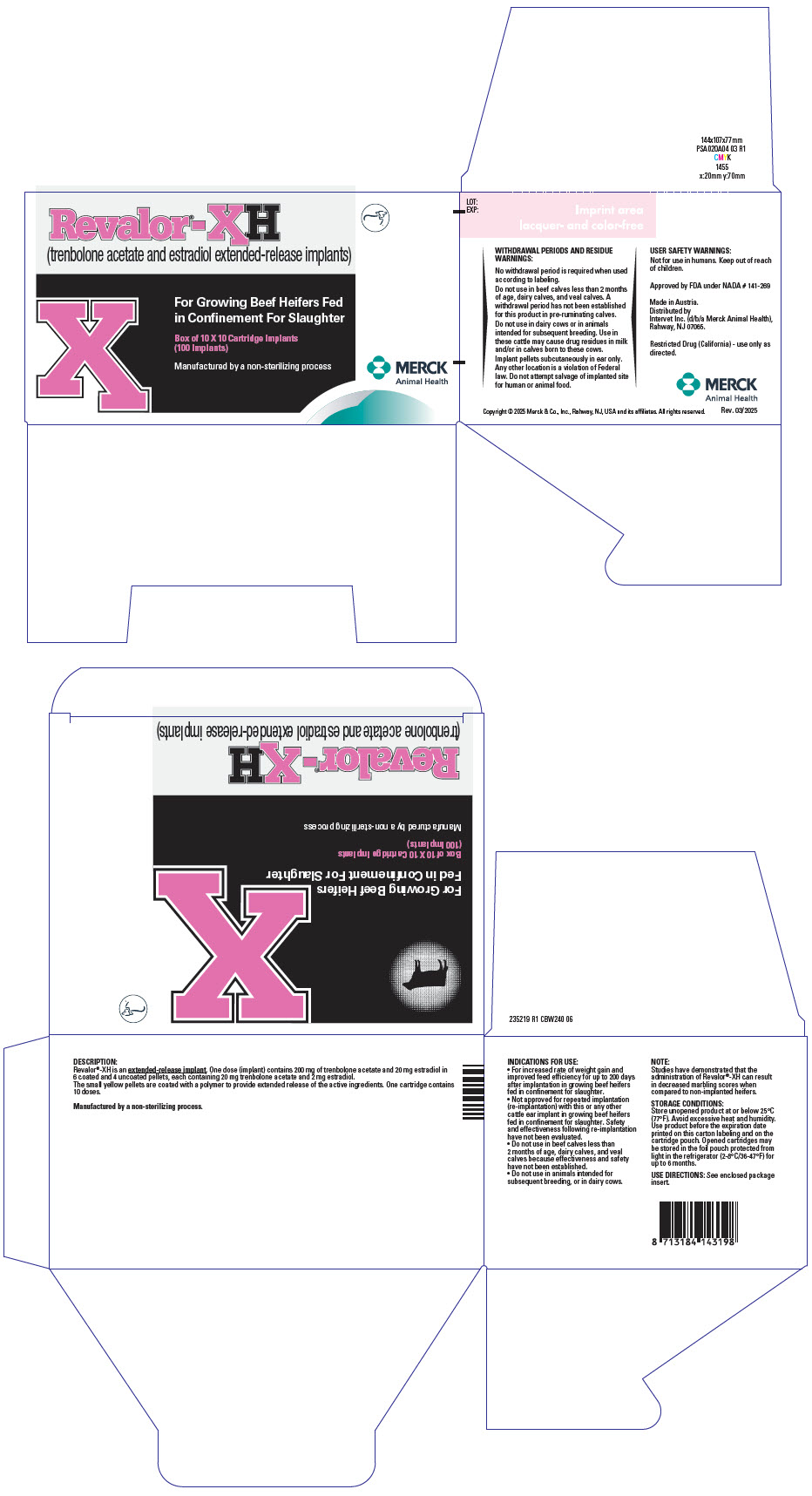 DRUG LABEL: Revalor XH
NDC: 57926-027 | Form: IMPLANT
Manufacturer: Merck Sharp & Dohme Corp.
Category: animal | Type: OTC ANIMAL DRUG LABEL
Date: 20250815

ACTIVE INGREDIENTS: TRENBOLONE ACETATE 200 mg/1 1; ESTRADIOL 20 mg/1 1
INACTIVE INGREDIENTS: MAGNESIUM STEARATE

Revalor®-XH
(trenbolone acetate and estradiol extended-release implants)

For Growing Beef Heifers Fed In Confinement For Slaughter

DESCRIPTION:

Revalor®-XH is an extended-release implant. One dose (implant) contains 200 mg of trenbolone acetate and 20 mg estradiol in 6 coated and 4 uncoated pellets, each containing 20 mg trenbolone acetate and 2 mg estradiol.

The small yellow pellets are coated with a polymer to provide extended release of the active ingredients. One cartridge contains 10 doses.

Manufactured by a non-sterilizing process.

INDICATIONS FOR USE:

For increased rate of weight gain and improved feed efficiency for up to 200 days after implantation in growing beef heifers fed in confinement for slaughter.

Not approved for repeated implantation (re-implantation) with this or any other cattle ear implant in growing beef heifers fed in confinement for slaughter. Safety and effectiveness following re-implantation have not been evaluated.

Do not use in beef calves less than 2 months of age, dairy calves, and veal calves because effectiveness and safety have not been established.

Do not use in animals intended for subsequent breeding, or in dairy cows.

NOTE:

Studies have demonstrated that the administration of Revalor®-XH can result in decreased marbling scores when compared to non-implanted heifers.

DIRECTIONS:

The cartridge is designed to be used with a special implanting tool. The special implanting tool is available from Intervet Inc. Ten doses (implants) are in each cartridge. The implant is placed under the skin on the posterior aspect of the ear (see SITE OF IMPLANTATION and METHOD OF USE sections).

With the animal suitably restrained, the skin on the outer surface of the ear should be cleaned. The implant is then administered by the method shown in the diagram below:

Fig. 1: Ear of Bovine Ready for Implantation

SITE OF IMPLANTATION:

After appropriately restraining the animal to allow access to the ear, cleanse the skin at the implant needle puncture site. It is subcutaneous between the skin and cartilage on the back side of the ear and below the midline of the ear. The implant must not be placed closer to the head than the edge of the cartilage ring farthest from the head. The location of insertion of the needle is a point toward the tip of the ear and at least a needle length away from the intended deposition site. Care should be taken to avoid injuring the major blood vessels or cartilage of the ear.

Fig. 2: Rear View of the Bovine Ear Showing the Site for Insertion of the Implanter needle

METHOD OF USE:

1. Do not remove the cap of the cartridge containing the implants.
2. Place the cartridge (D) with the capped end to the front into slot at the top of the implanter magazine marked (A) on the diagram.
3. Gently push the cartridge into the slot until it clicks into place.
4. The implanter is then ready for use.
5. Take the ear of the animal firmly with the free hand in the manner shown in Fig. 1. Then insert the needle into the subcutaneous tissue at the point indicated in Fig. 2.
6. After inserting the needle to its full extent, squeeze the trigger (E) gradually. Allow the pellets of the implant to be deposited in a single row.
7. Withdraw the implanter. This will advance the cartridge one groove in the magazine and the next implant is now ready for use.
8. When all the implants have been administered, the cartridge will discharge out the bottom of the magazine and may be replaced by a new one.
9. To change the needle, loosen the needle locking nut labeled (F) in Fig. 3 and replace the needle. Tighten the nut finger tight and the implanter is ready for use.

Fig. 3: Diagram of the Implanter and Cartridge

WITHDRAWAL PERIODS AND RESIDUE WARNINGS:

No withdrawal period is required when used according to labeling.

Do not use in beef calves less than 2 months of age, dairy calves, and veal calves. A withdrawal period has not been established for this product in pre-ruminating calves.

Do not use in dairy cows or in animals intended for subsequent breeding. Use in these cattle may cause drug residues in milk and/or in calves born to these cows.

Implant pellets subcutaneously in ear only. Any other location is a violation of Federal law. Do not attempt salvage of implanted site for human or animal food.

USER SAFETY WARNINGS:

Not for use in humans. Keep out of reach of children.

QUESTIONS/COMMENTS?

For a copy of the Safety Data Sheet or to report side effects, contact Merck Animal Health Technical Services at 1-800-211-3573. For additional information about reporting side effects for animal drugs, contact FDA at 1-888-FDA-VETS or at http://www.fda.gov/reportanimalae

STORAGE CONDITIONS:

Store unopened product at or below 25°C (77°F). Avoid excessive heat and humidity. Use product before the expiration date printed on the carton labeling and on the cartridge pouch. Opened cartridges may be stored in the foil pouch protected from light in the refrigerator (2-8°C/36-47°F) for up to 6 months.

HOW SUPPLIED:

Box of 10 cartridges, each containing 10 implants per cartridge (100 implants total).

Made in Austria.

Distributed by
Intervet Inc. (d/b/a Merck Animal Health),
Rahway, NJ 07065.

Restricted Drug (California) – use only as directed.

Approved by FDA under NADA # 141-269

Copyright © 2025 Merck & Co., Inc., Rahway, NJ, USA and its affiliates. All rights reserved.

Rev. 03/2025

235217 R1

PRINCIPAL DISPLAY PANEL - 10 x 10 Cartridge Implant Carton

Revalor®-XH
(trenbolone acetate and estradiol extended-release implants)

For Growing Beef Heifers Fed
in Confinement For Slaughter

Box of 10 X 10 Cartridge Implants
(100 Implants)

Manufactured by a non-sterilizing process

MERCK
Animal Health